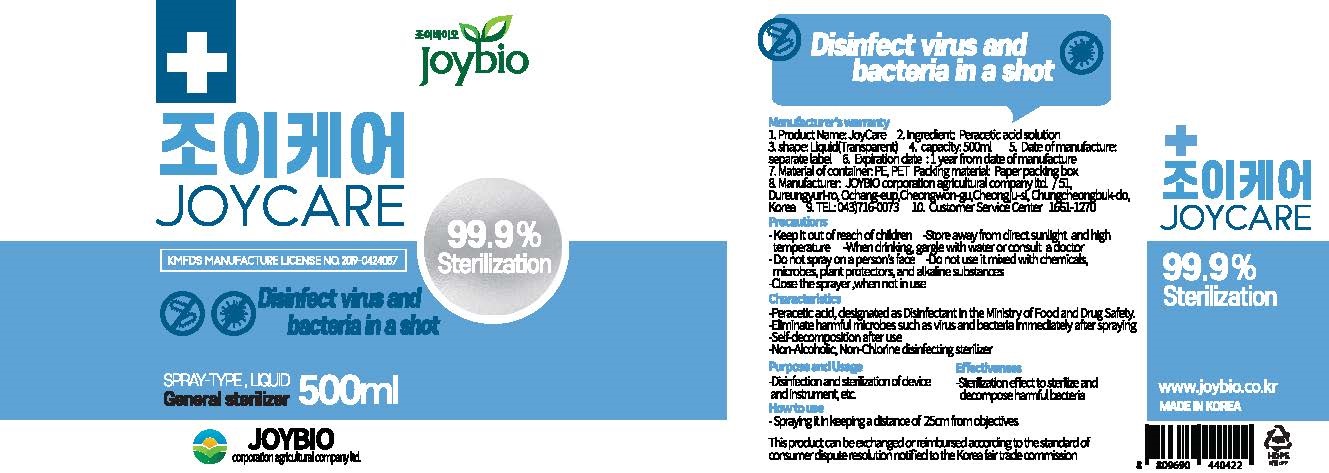 DRUG LABEL: JOYCARE
NDC: 76993-0001 | Form: LIQUID
Manufacturer: Joybio Corporation Agricultural Company Ltd
Category: otc | Type: HUMAN OTC DRUG LABEL
Date: 20200521

ACTIVE INGREDIENTS: PERACETIC ACID 0.26 g/100 mL
INACTIVE INGREDIENTS: WATER

Drug Facts

ACTIVE INGREDIENT

PARACETIC ACID

INACTIVE INGREDIENT

water,

KEEP OUT OF REACH OF THE CHILDREN

PURPOSE

general disinfectant

INDICATIONS AND USAGE

spraying it in keeping a distance of 25cm from objectives

WARNINGS

For external use only.

Flammable, keep away from fire or flame.

When using this product keep out of eyes. If contact with eyes occurs, rinse promptly and thoroughly with water.

Stop use and ask a doctor if significant irritation or sensitization develops.

Keep out of reach of children. If swallowed, get medical help or contact a Poison Control Center right away.

DOSAGE AND ADMINISTRATION

for external use only